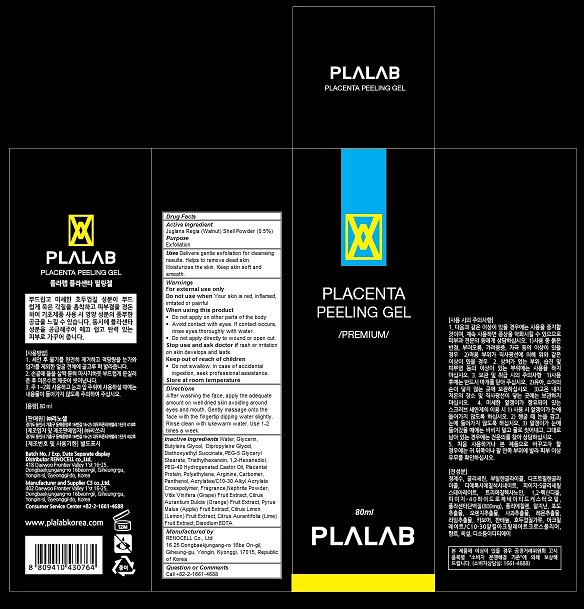 DRUG LABEL: Plalab Placenta Peeling
NDC: 70326-101 | Form: GEL
Manufacturer: RENOCELL Co., Ltd
Category: otc | Type: HUMAN OTC DRUG LABEL
Date: 20151223

ACTIVE INGREDIENTS: JUGLANS REGIA SHELL 0.005 1/80 mL
INACTIVE INGREDIENTS: WATER; Glycerin; Butylene Glycol; Dipropylene Glycol; Diethoxyethyl Succinate; PEG-5 Glyceryl Stearate; Triethylhexanoin; 1,2-Hexanediol; POLYOXYL 40 HYDROGENATED CASTOR OIL; SUS SCROFA PLACENTA; HIGH DENSITY POLYETHYLENE; ARGININE; CARBOXYPOLYMETHYLENE; Panthenol; CARBOMER INTERPOLYMER TYPE A (ALLYL SUCROSE CROSSLINKED); WINE GRAPE; ORANGE; APPLE; LEMON; LIME (CITRUS); EDETATE DISODIUM

Plalab Placenta Peeling Gel